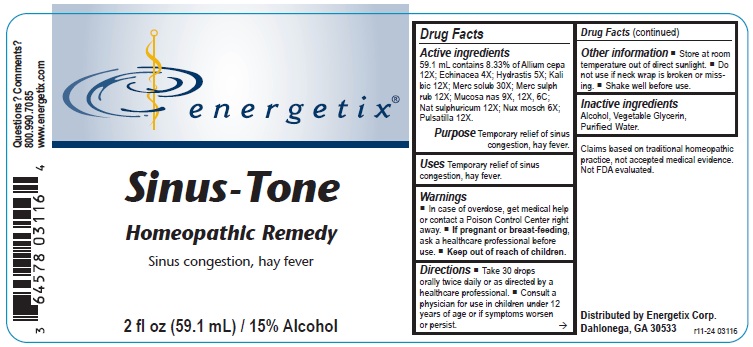 DRUG LABEL: Sinus-Tone
NDC: 64578-0154 | Form: LIQUID
Manufacturer: Energetix Corporation
Category: homeopathic | Type: HUMAN OTC DRUG LABEL
Date: 20250711

ACTIVE INGREDIENTS: ONION 12 [hp_X]/59.1 mL; ECHINACEA, UNSPECIFIED 4 [hp_X]/59.1 mL; GOLDENSEAL 5 [hp_X]/59.1 mL; POTASSIUM DICHROMATE 12 [hp_X]/59.1 mL; MERCURIUS SOLUBILIS 30 [hp_X]/59.1 mL; MERCURIC SULFIDE 12 [hp_X]/59.1 mL; SUS SCROFA NASAL MUCOSA 9 [hp_X]/59.1 mL; SODIUM SULFATE 12 [hp_X]/59.1 mL; NUTMEG 6 [hp_X]/59.1 mL; PULSATILLA VULGARIS 12 [hp_X]/59.1 mL
INACTIVE INGREDIENTS: WATER; GLYCERIN; ALCOHOL

Sinus-Tone

ACTIVE INGREDIENT

Active ingredients59.1 mL contains 8.33% of: Allium cepa 12X; Echinacea 4X; Hydrastis 5X; Kali bic 12X; Merc solub 30X; Merc sulph rub
12X; Mucosa nas 9X, 12X, 6C; Nat sulphuricum 12X; Nux mosch 6X; Pulsatilla 12X.

Claims based on traditional homeopathic practice, not accepted medical evidence. Not FDA evaluated.

Uses

Temporary relief of sinus congestion, hay fever.

Warnings

- In case of overdose, get medical help or contact a Poison Control Center right away.
- If pregnant or breast-feeding, ask a healthcare professional before use.

- Keep out of reach of children.

Directions

- Take 30 drops orally twice daily or as directed by a healthcare professional.
- Consult a physician for use in children under 12 years of age or if symptoms worsen or persist.

Other information

- Store at room temperature out of direct sunlight.
- Do not use if neck wrap is broken or missing.
- Shake well before use.

Inactive ingredients

Alcohol, Vegetable Glycerin, Purified Water.

QUESTIONS

Distributed by

Energetix Corp.

Dahlonega, GA 30533

Questions? Comments?

800.990.7085

www.energetix.com

PACKAGE LABEL

energetix

Sinus-Tone

Homeopathic Remedy

Sinus congestion, hay fever

2 fl oz (59.1 mL) / 15% Alcohol

PURPOSE

PurposeTemporary relief of sinus congestion, hay fever.